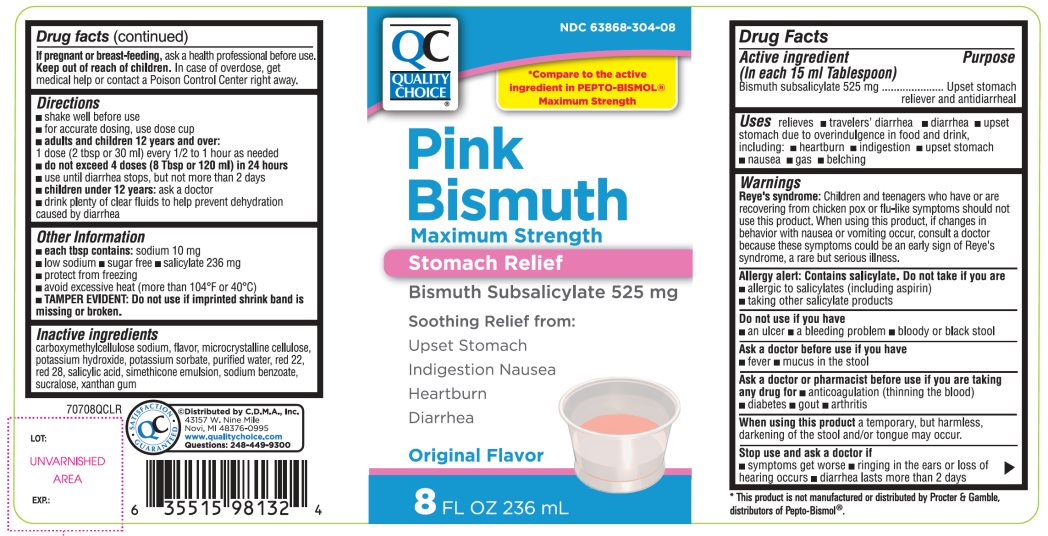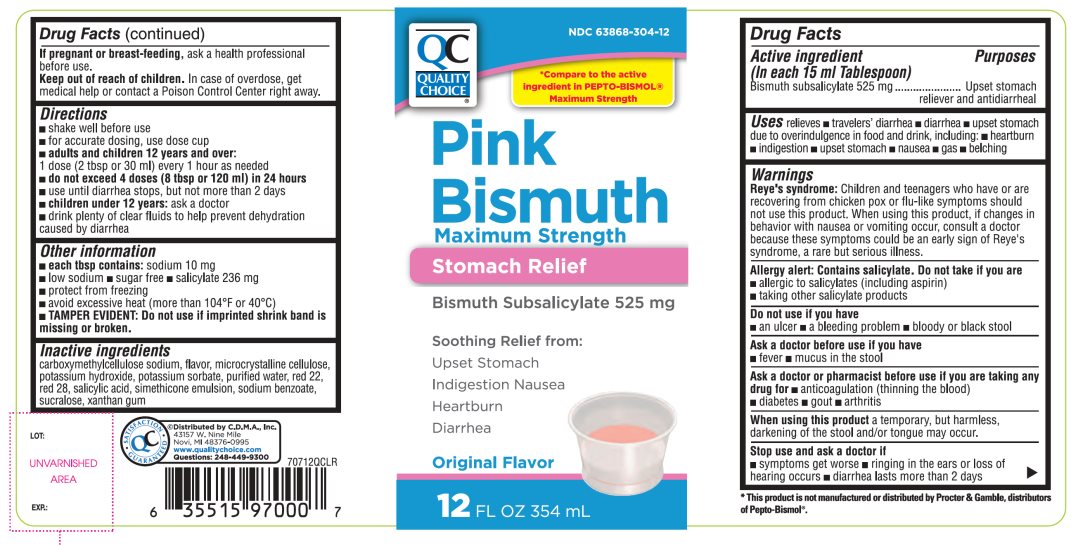 DRUG LABEL: QC Stomach Relief

NDC: 63868-304 | Form: LIQUID
Manufacturer: QUALITY CHOICE (CHAIN DRUG MARKETING ASSOCIATION)
Category: otc | Type: HUMAN OTC DRUG LABEL
Date: 20251204

ACTIVE INGREDIENTS: BISMUTH SUBSALICYLATE 525 mg/15 mL
INACTIVE INGREDIENTS: CARBOXYMETHYLCELLULOSE SODIUM, UNSPECIFIED; MICROCRYSTALLINE CELLULOSE; POTASSIUM HYDROXIDE; POTASSIUM SORBATE; WATER; D&C RED NO. 22; D&C RED NO. 28; SALICYLIC ACID; DIMETHICONE, UNSPECIFIED; SODIUM BENZOATE; SUCRALOSE; XANTHAN GUM

Quality Choice Max Strength Bismuth Subsalicylate 525mg

Active ingredient (in each 15 mL)

Bismuth subsalicylate 525 mg

Purpose

Upset stomach reliever/Antidiarrheal

Uses

relieves

- travelers' diarrhea
- diarrhea
- upset stomach due to overindulgence in food and drink, including:
  - heartburn
  - indigestion
  - upset stomach
  - nausea
  - gas
  - belching

Warnings

Reye's syndrome: Children and teenagers who have or are recovering from chicken pox or flu-like symptoms should not use this product. When using this product, if changes in behavior with nausea and vomiting occur, consult a doctor because these symptoms could be an early sign of Reye's syndrome, a rare but serious illness.

Allergy alert: Contains salicylate. Do not take if you are

- allergic to salicylates (including aspirin)
- taking other salicylate products

Do not use

if you have

- an ulcer
- a bleeding problem
- bloody or black stool

Ask a doctor before use if you have

- fever
- mucus in the stool

Ask a doctor or pharmacist before use if you are

taking any drug for

- anticoagulation (thinning the blood)
- diabetes
- gout
- arthritis

When using this product

a temporary, but harmless, darkening of the stool and/or tongue may occur.

Stop use and ask a doctor if

- symptoms get worse
- ringing in the ears or loss of hearing occurs
- diarrhea lasts more than 2 days

If pregnant or breast-feeding,

ask a health professional before use.

Keep out of reach of children.

In case of overdose, get medical help or contact a Poison Control Center right away. (1-800-222-1222)

Directions

- shake well before use
- For accurate dosing, use dose cup
- adults and children 12 years and over:
  - 1 dose (2 tbsp. or 30 ml) every 1 hour as needed
  - do not exceed 4 doses (8tbsp or 120 mL) in 24 hours
  - use until diarrhea stops but not more than 2 days
- children under 12 years:ask a doctor
- drink plenty of clear fluids to help prevent dehydration caused by diarrhea

Other information

- each tbsp. contains:sodium 10 mg
- low sodium
- sugar free
- salicylate 236 mg
- protect from freezing
- avoid excessive heat (more than 104ºF or 40ºC)
- TAMPER EVIDENT: Do not use if imprinted shrink band is missing or broken

Inactive ingredients

Carboxymethylcellulose sodium, flavor, microcrystalline cellulose, potassium hydroxide, potassium sorbate, purified water, red 22, red 28, salicylic acid, simethicone emulsion, sodium benzoate, sucralose, xanthan gum.

Principal Display Panel

Compare to the active ingredient in Pepto-Bismol® Maximum Strength

Pink Bismuth

Maximum Strength

Stomach Relief

Bismuth Subsalicylate 525 mg

Soothing Relief from:

Upset Stomach

Indigestion Nausea

Heartburn

Diarrhea

Original Flavor

FL OZ (mL)

QC SATISFACTION GURANTEED

*This product is not manufactured or distributed by The Procter & Gamble, distributors of Pepto-Bismol®.

Distributed by C.D.M.A., Inc.

43157 W. Nine Mile

Novi, MI 48376-0995

www.qualitychoice.com

Questions: 248-449-9300